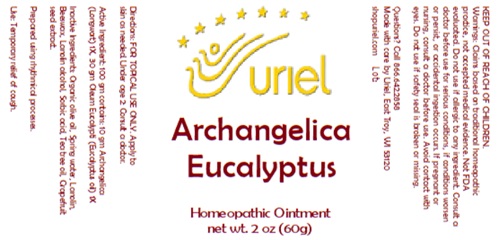 DRUG LABEL: Archangelica Eucalyptus
NDC: 48951-1387 | Form: OINTMENT
Manufacturer: Uriel Pharmacy Inc.
Category: homeopathic | Type: HUMAN OTC DRUG LABEL
Date: 20250627

ACTIVE INGREDIENTS: ANGELICA ARCHANGELICA ROOT 1 [hp_X]/1 g; EUCALYPTUS OIL 1 [hp_X]/1 g
INACTIVE INGREDIENTS: OLIVE OIL; TEA TREE OIL; WATER; LANOLIN; YELLOW WAX; CITRUS PARADISI SEED; LANOLIN ALCOHOLS; SORBIC ACID

Archangelica Eucalyptus

INDICATIONS AND USAGE

Directions: FOR TOPICAL USE ONLY.

DOSAGE AND ADMINISTRATION

Apply to skin as needed. Under age 2: Consult a doctor.

Active Ingredient: 100 gm contains: 10 gm Archangelica (Longwort) 1X, 30 gm Oleum Eucalypti (Eucalyptus oil) 1X

INACTIVE INGREDIENT

Inactive Ingredients: Organic olive oil, Spring water, Lanolin, Beeswax, Lanolin alcohol, Sorbic acid, Tea tree oil, Grapefruit seed extract.

Prepared using rhythmical processes.

PURPOSE

Use: Temporary relief of cough

KEEP OUT OF REACH OF CHILDREN.

WARNINGS

Warnings: Claims based on traditional homeopathic practice, not accepted medical evidence. Not FDA evaluated. Do not use if allergic to any ingredient. Consult a doctor before use for serious conditions, if conditions worsen or persist, or accidental ingestion occurs. If pregnant or nursing, consult a doctor before use. Avoid contact with eyes. Do not use if safety seal is broken or missing.

Questions? Call 866.642.2858
Made with care by Uriel, East Troy, WI 53120
shopuriel.com Lot: